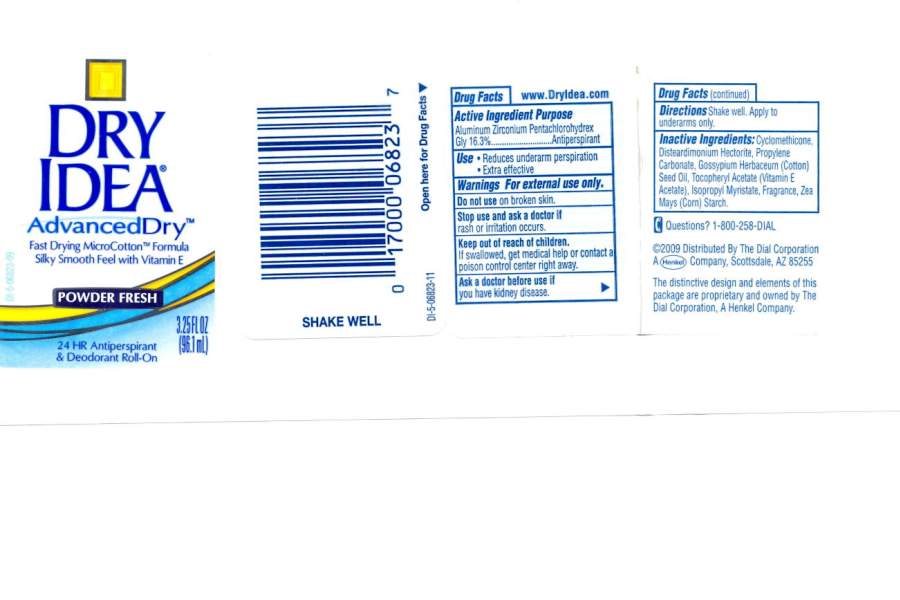 DRUG LABEL: Dry Idea AD Antiperspirant Roll-On Powder Fresh
NDC: 54340-682 | Form: LIQUID
Manufacturer: The Dial Corporation
Category: otc | Type: HUMAN OTC DRUG LABEL
Date: 20110614

ACTIVE INGREDIENTS: ALUMINUM ZIRCONIUM PENTACHLOROHYDREX GLY 16.3 mL/96.1 mL
INACTIVE INGREDIENTS: CYCLOMETHICONE 5 36.975 mL/96.1 mL; PROPYLENE CARBONATE 1.0 mL/96.1 mL; TOCOPHEROL 0.10 mL/96.1 mL; LEVANT COTTONSEED OIL 0.0485 mL/96.1 mL; ISOPROPYL MYRISTATE 0.0485 mL/96.1 mL

Dry Idea Advanced Dry 24HR Antiperspirant and Deodorant Roll-On Powder Fresh

ACTIVE INGREDIENT

Aluminum Zirconium Pentachlorohydrex Gly 16.3%

PURPOSE

USE: Reduces underarm perspiration. Extra effective

Warnings.....For external use only.

Do not use on broken skin.

Stop use and ask a doctor is rash or irritation occurs.

Keep out of reach of children. If swallowed, get medical help or contact a poison control center right away.

Ask a doctor before use if you have kidney disease.

INDICATIONS AND USAGE

Directions: Shake well. Apply to underarms only.

INACTIVE INGREDIENT

Inactive Ingredients: Cyclomethicone, Disteardimonium Hectorite, Propylene Carbonate, Gossypium Herbaceum (Cotton) Seed Oil, Tocopheryl Acetate (Vitamin E Acetate), Isopropyl Myristate, Fragrance, Zea Mays (Corn) Starch.

Questions: 1-800-258-DIAL

HOW SUPPLIED

2009 Distributed By The Dial Corporation, A Henkel Company, Scottsdale, AZ 85255. The distinctive design and elements of this package ae proprietary and owned by the Dial Corporation, A Henkel Company.

DOSAGE AND ADMINISTRATION

DIRECTIONS: Shake well. Apply to underarms only.